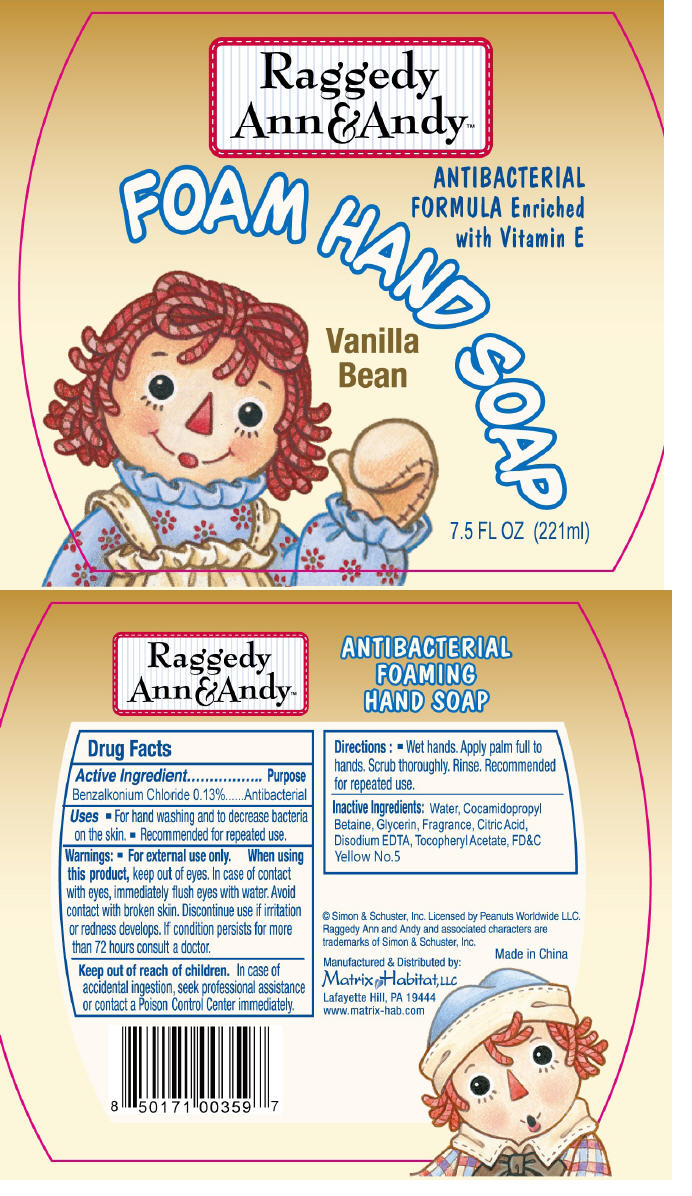 DRUG LABEL: Raggedy Ann and Andy Foam 
NDC: 75878-003 | Form: SOAP
Manufacturer: My Habitat Brands LLC
Category: otc | Type: HUMAN OTC DRUG LABEL
Date: 20101206

ACTIVE INGREDIENTS: Benzalkonium Chloride 0.0013 g/1 mL
INACTIVE INGREDIENTS: Water; Cocamidopropyl Betaine; Glycerin; Citric Acid Monohydrate; Edetate Disodium; FD&C Yellow No. 5

Raggedy
Ann&Andy™
FOAM HAND SOAP
Vanilla
Bean

Drug Facts

Active Ingredient

Benzalkonium Chloride 0.13%

Purpose

Antibacterial

Uses

- For hand washing and to decrease bacteria on the skin.
- Recommended for repeated use.

Warnings

- For external use only.

When using this product, keep out of eyes. In case of contact with eyes, immediately flush eyes with water. Avoid contact with broken skin.

STOP USE

Discontinue use if irritation or redness develops. If condition persists for more than 72 hours consult a doctor.

Keep out of reach of children. In case of accidental ingestion, seek professional assistance or contact a Poison Control Center immediately.

Directions

- Wet hands. Apply palm full to hands. Scrub thoroughly. Rinse. Recommended for repeated use.

Inactive Ingredients

Water, Cocamidopropyl Betaine, Glycerin, Fragrance, Citric Acid, Disodium EDTA, Tocopheryl Acetate, FD&C Yellow No.5

PRINCIPAL DISPLAY PANEL - 221ml Bottle Label

Raggedy
Ann&Andy™

ANTIBACTERIAL
FORMULA Enriched
with Vitamin E

FOAM HAND SOAP

Vanilla
Bean

7.5 FL OZ (221ml)